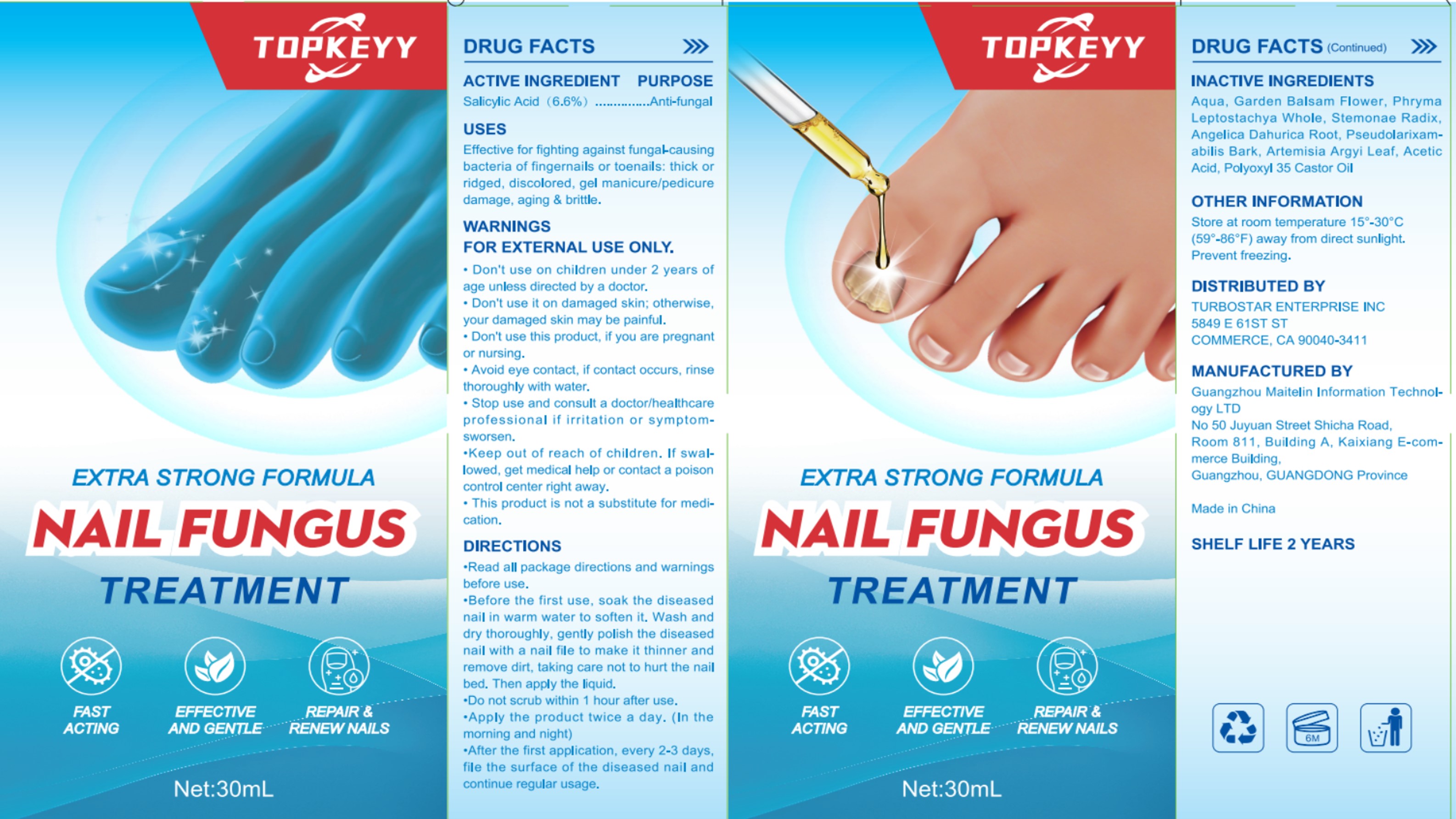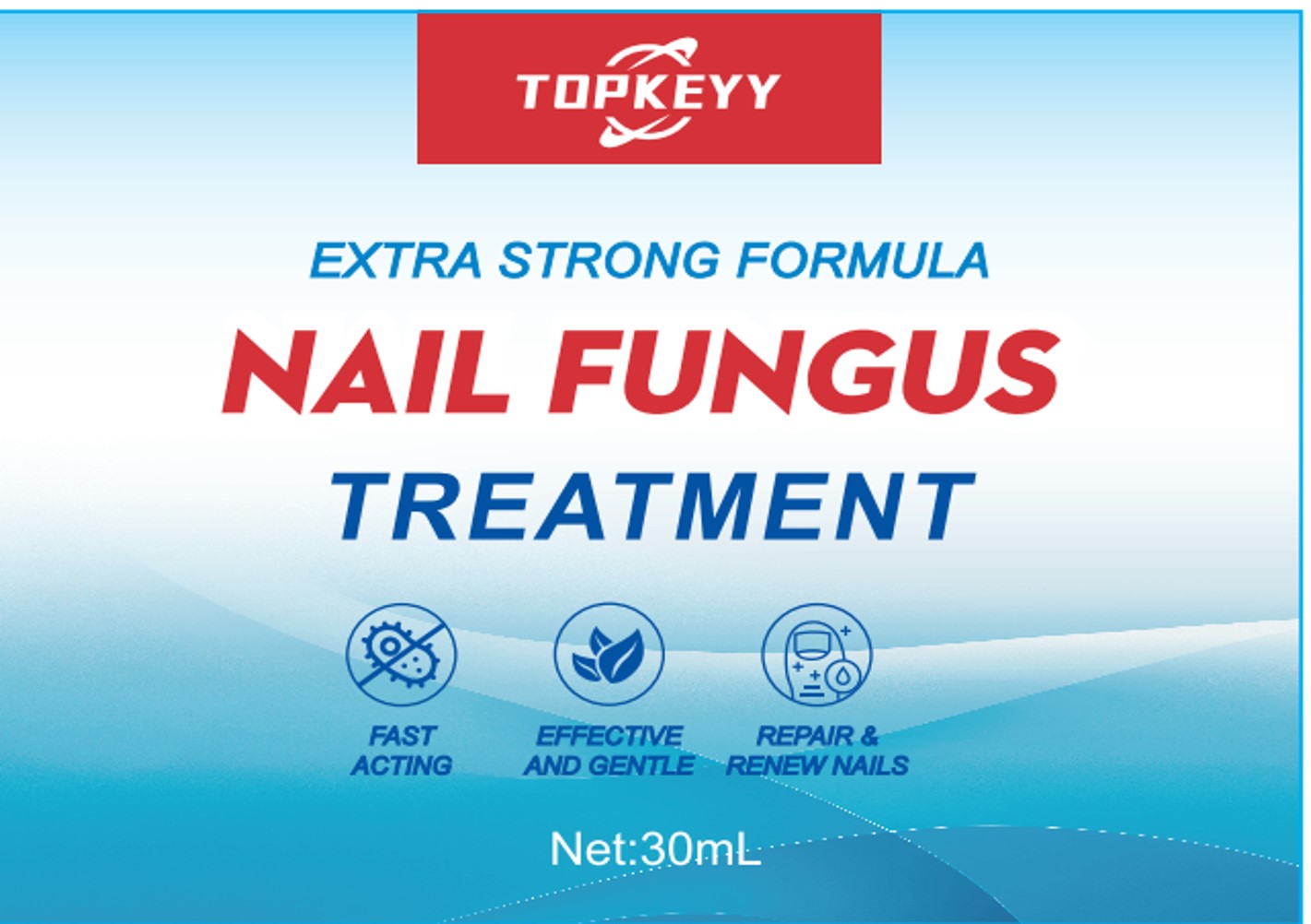 DRUG LABEL: Nail Fungus Treatment
NDC: 84257-101 | Form: LIQUID
Manufacturer: Guangzhou Maitelin Information Technology Co., Ltd.
Category: otc | Type: HUMAN OTC DRUG LABEL
Date: 20240410

ACTIVE INGREDIENTS: SALICYLIC ACID 6.6 g/100 mL
INACTIVE INGREDIENTS: PHRYMA LEPTOSTACHYA WHOLE; ANGELICA DAHURICA ROOT; PSEUDOLARIX AMABILIS BARK; WATER; STEMONA SESSILIFOLIA ROOT; IMPATIENS BALSAMINA FLOWER; ARTEMISIA ARGYI LEAF; ACETIC ACID; POLYOXYL 35 CASTOR OIL

Nail Fungus Treatment

Nail Fungus Treatment

ACTIVE INGREDIENT

Salicylic Acid 6.6%

PURPOSE

Anti-fungal

INDICATIONS AND USAGE

Effective for fighting against fungalcausingbacteria of fingernails or toenails: thick orridged, discolored, gel manicure/pedicuredamage, aging & brittle.

WARNINGS

FOR EXTERNAL USE ONLY.

DO NOT USE

Don't use on children under 2 years ofage unless directed by a doctor.
Don't use it on damaged skin; otherwise, your damaged skin may be painful.
Don't use this product, if you are pregnantor nursing.

WHEN USING

Avoid eye contact, if contact occurs, rinsethoroughly with water.

Stop use and consult a doctor/healthcareprofessional if irritation or symptom-sworsen.

Keep out of reach of children. If swal-lowed, get medical help or contact a poisoncontrol center right away.

DOSAGE AND ADMINISTRATION

Read all package directions and warningsbefore use.
Before the first use, soak the diseasednail in warm water to soften it. Wash anddry thoroughly, gently polish the diseasednail with a nail file to make it thinner andremove dirt, taking care not to hurt the nailbed. Then apply the liquid.
Do not scrub within 1 hour after use.
Apply the product twice a day. (In themorning and night)
After the first application, every 2-3 daysfile the surface of the diseased nail andcontinue regular usage.

STORAGE AND HANDLING

Store at room temperature 15°-30°C(59°-86°F) away from direct sunlight.Prevent freezing.

INACTIVE INGREDIENT

AQUA
GARDEN BALSAM FLOWER
PHRYMA LEPTOSTACHYA WHOLE
STEMONAE RADIX
ANGELICA DAHURICA ROOT
PSEUDOLARIXAMABILIS BARK
ARTEMISIA ARGYI LEAF
ACETIC ACID
POLYOXYL 35 CASTOR OIL